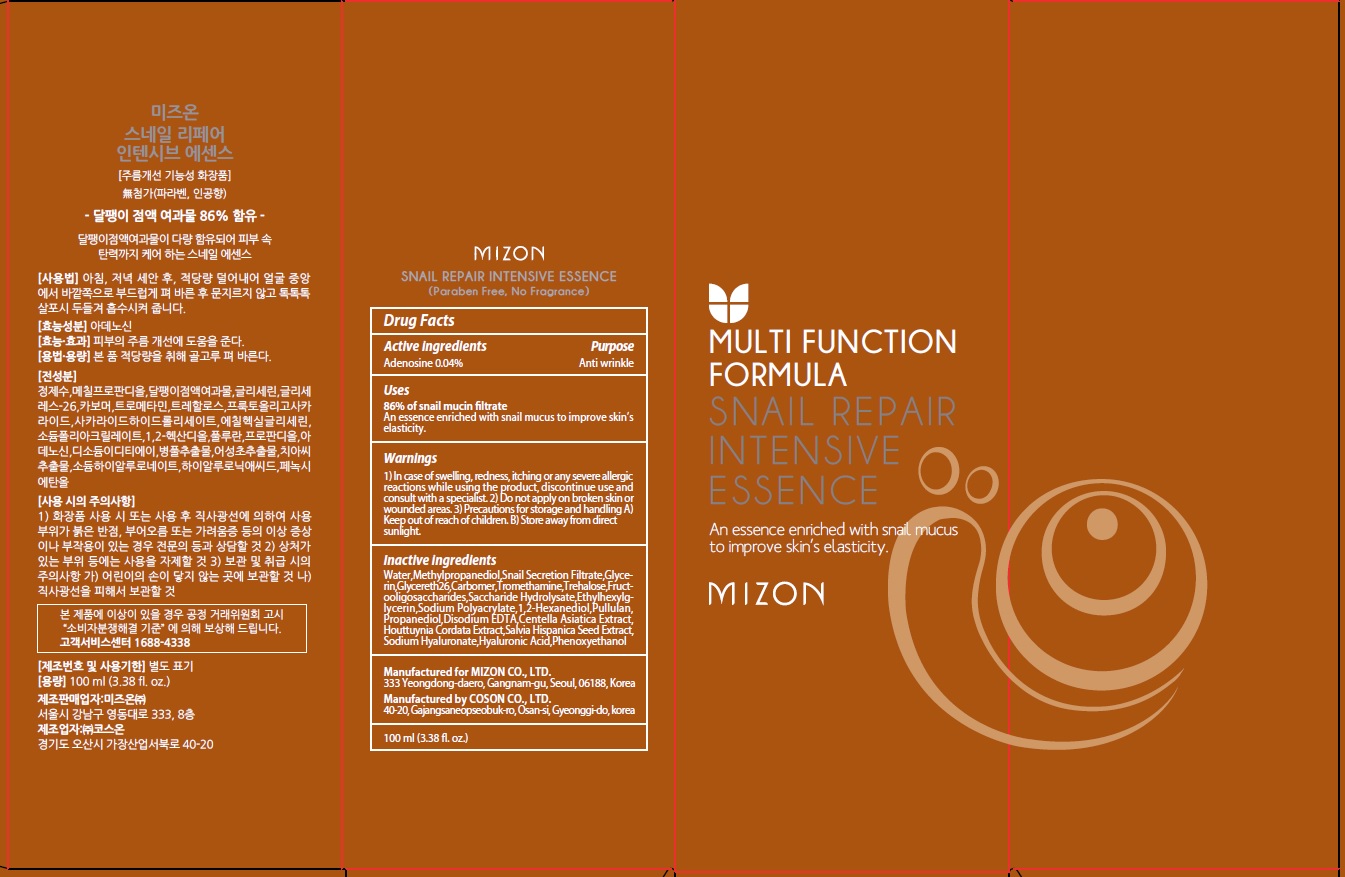 DRUG LABEL: MIZON SNAIL REPAIR INTENSIVE ESSENCE
NDC: 57718-210 | Form: LIQUID
Manufacturer: MIZON CO.,LTD.
Category: otc | Type: HUMAN OTC DRUG LABEL
Date: 20180719

ACTIVE INGREDIENTS: Adenosine 0.04 g/100 mL
INACTIVE INGREDIENTS: Water; Methylpropanediol

ACTIVE INGREDIENT

Active ingredients: Adenosine 0.04%

INACTIVE INGREDIENT

Inactive ingredients:

Water,Methylpropanediol,Snail Secretion Filtrate,Glycerin,Glycereth26,Carbomer,Tromethamine,Trehalose,Fructooligosaccharides,Saccharide Hydrolysate,Ethylhexylglycerin,Sodium Polyacrylate,1,2-Hexanediol,Pullulan,Propanediol,Disodium EDTA, Centella Asiatica Extract,Houttuynia Cordata Extract,Salvia Hispanica Seed Extract,Sodium Hyaluronate,Hyaluronic Acid,Phenoxyethanol

PURPOSE

Purpose: Anti wrinkle

WARNINGS

1) In case of swelling, redness, itching or any severe allergic reactions while using the product, discontinue use and consult with a specialist. 2) Do not apply on broken skin or wounded areas. 3) Precautions for storage and handling A) Keep out of reach of children. B) Store away from direct sunlight.

KEEP OUT OF REACH OF CHILDREN

Uses

86% of snail mucin filtrate.

An essence enriched with snail mucus to improve skin’s elasticity.

Directions

After cleansing, apply the essence over your face twice daily, morning and evening. Pat gently for a better absorption of the product